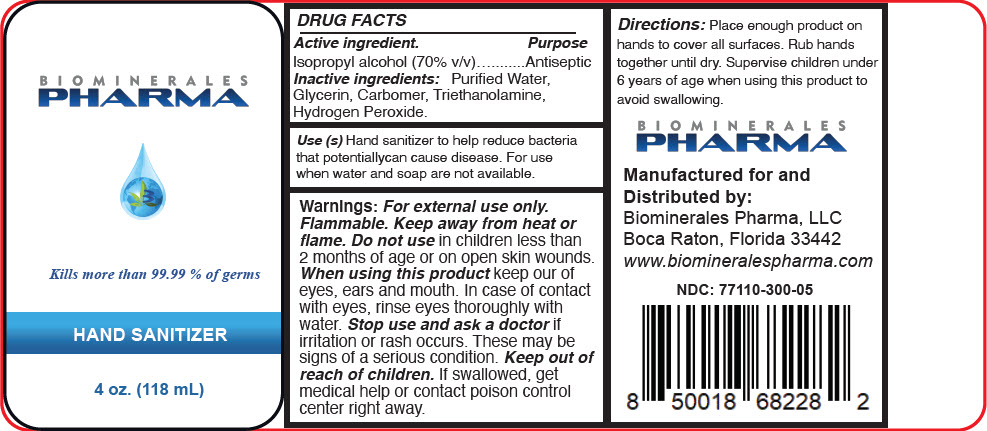 DRUG LABEL: HAND SANITIZER
NDC: 77110-300 | Form: GEL
Manufacturer: Biominerales Pharma, LLC
Category: otc | Type: HUMAN OTC DRUG LABEL
Date: 20200709

ACTIVE INGREDIENTS: ISOPROPYL ALCOHOL 70 mL/100 mL
INACTIVE INGREDIENTS: WATER; GLYCERIN; CARBOMER HOMOPOLYMER, UNSPECIFIED TYPE; TROLAMINE; HYDROGEN PEROXIDE

HAND SANITIZER

DRUG FACTS

Active ingredient

Isopropyl alcohol (70% v/v)

Purpose

Antiseptic

Inactive ingredients

Purified Water, Glycerin, Carbomer, Triethanolamine, Hydrogen Peroxide.

Use (s)

Hand sanitizer to help reduce bacteria that potentially can cause disease. For use when water and soap are not available.

Warnings

For external use only. Flammable. Keep away from heat or flame.

Do not use in children less than 2 months of age or on open skin wounds.

When using this product keep our of eyes, ears and mouth. In case of contact with eyes, rinse eyes thoroughly with water.

Stop use and ask a doctor if irritation or rash occurs. These may be signs of a serious condition.

Keep out of reach of children. If swallowed, get medical help or contact poison control center right away.

Directions

Place enough product on hands to cover all surfaces. Rub hands together until dry. Supervise children under 6 years of age when using this product to avoid swallowing.

Manufactured for and
Distributed by:
Biominerales Pharma, LLC
Boca Raton, Florida 33442

PRINCIPAL DISPLAY PANEL - 118 mL Bottle Label

BIOMINERALES
PHARMA

Kills more than 99.99 % of germs

HAND SANITIZER

4 oz. (118 mL)